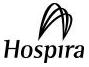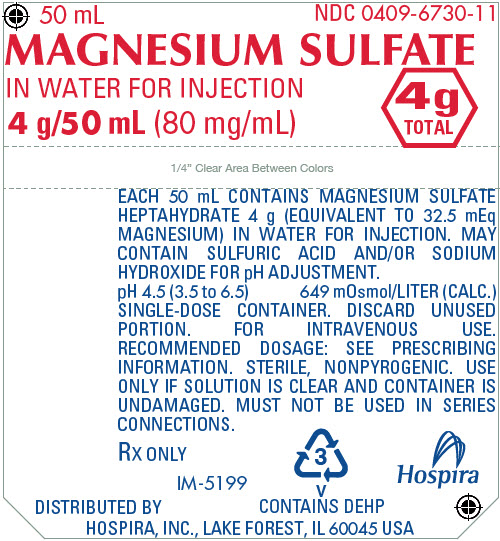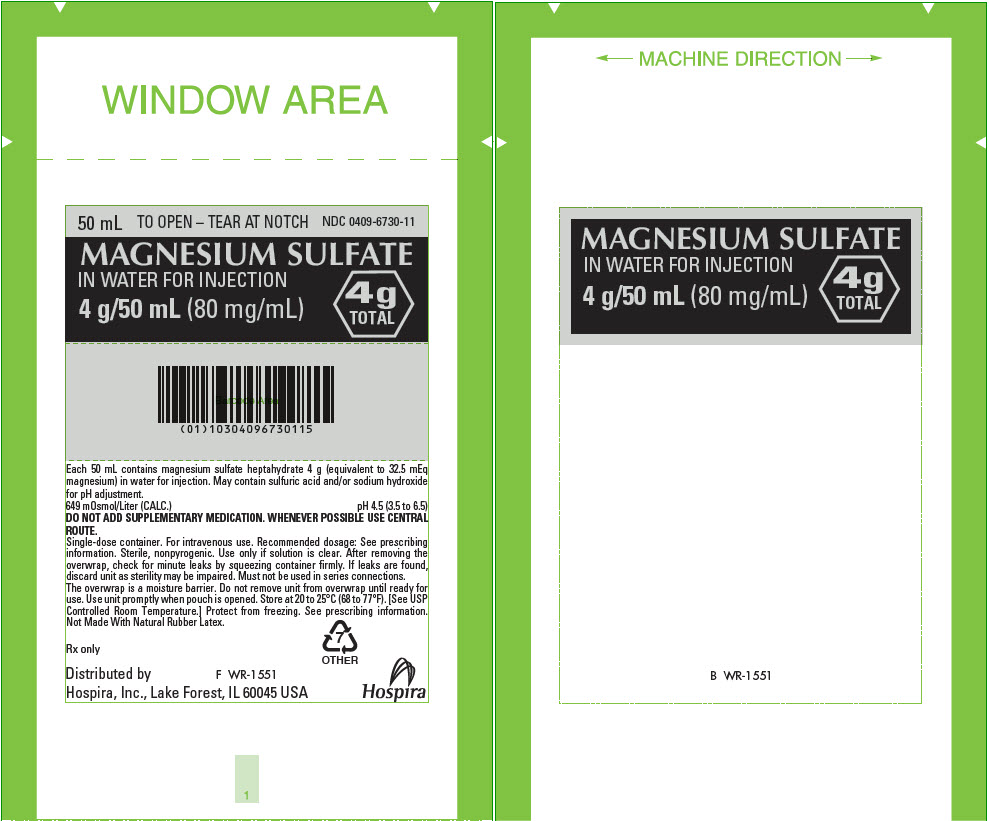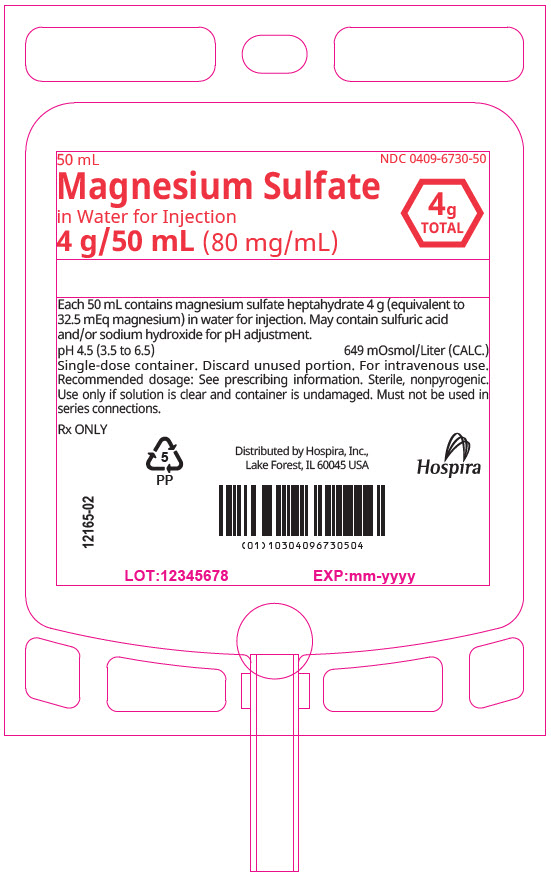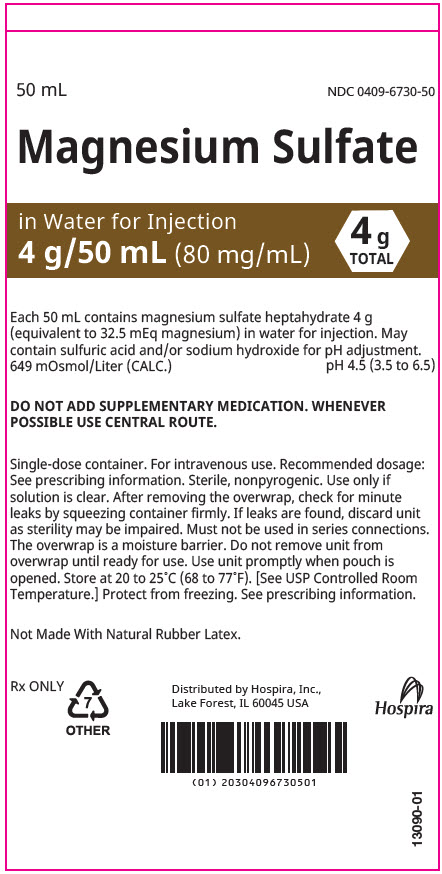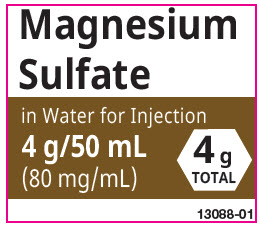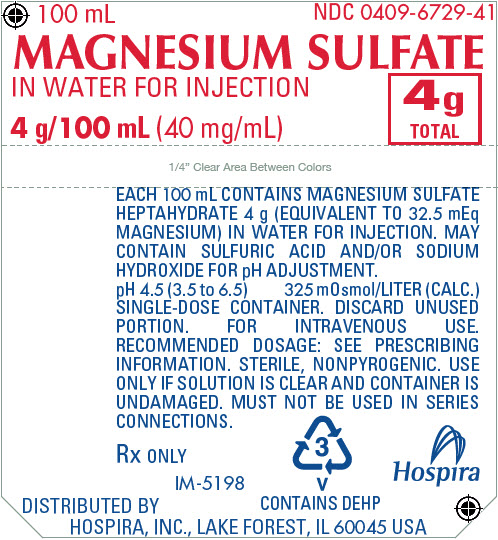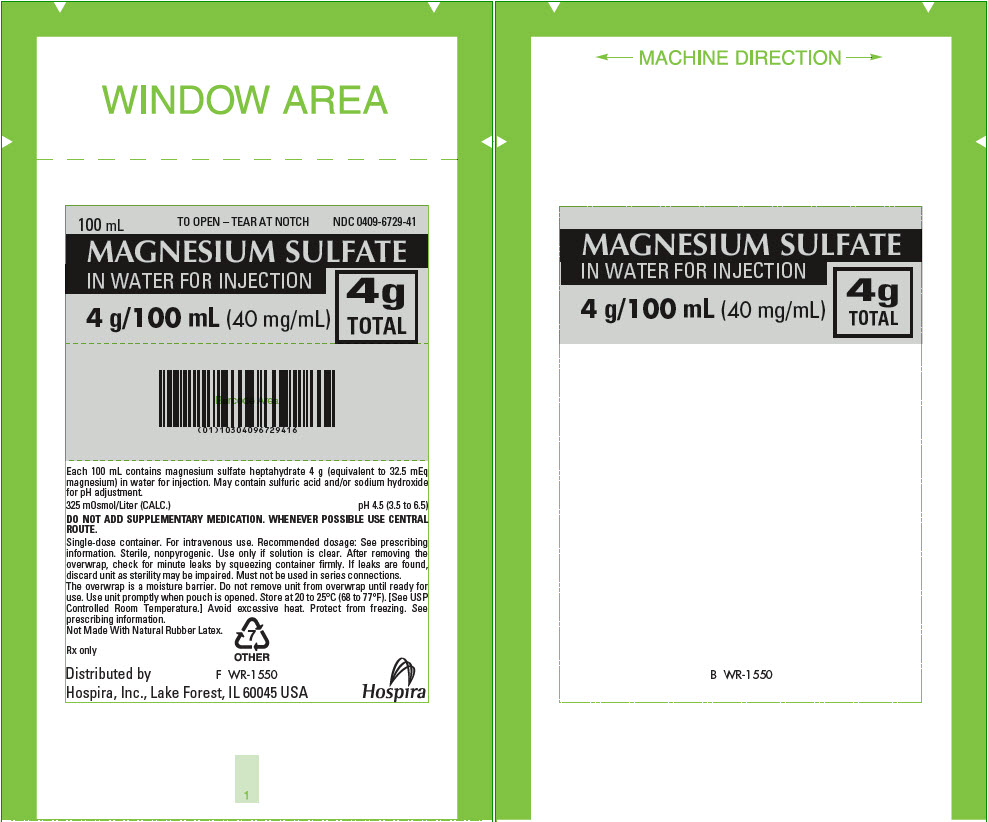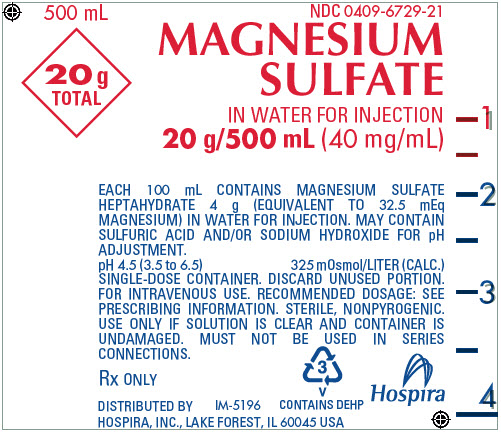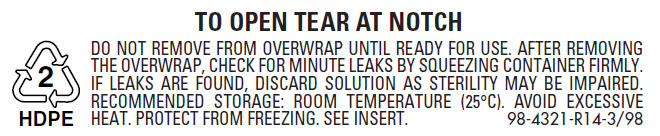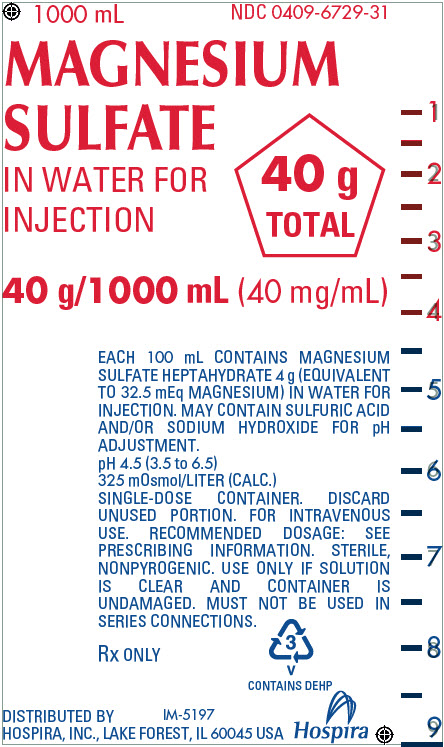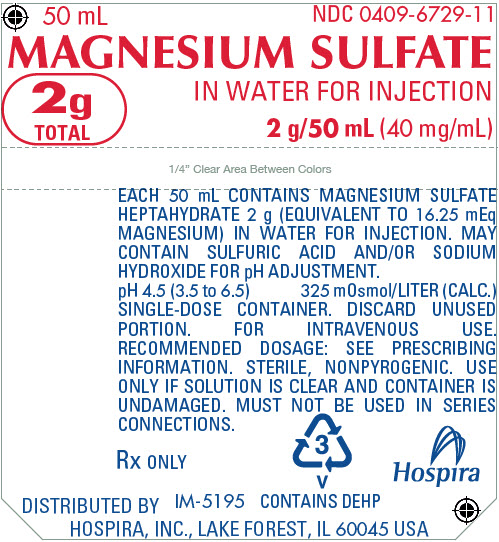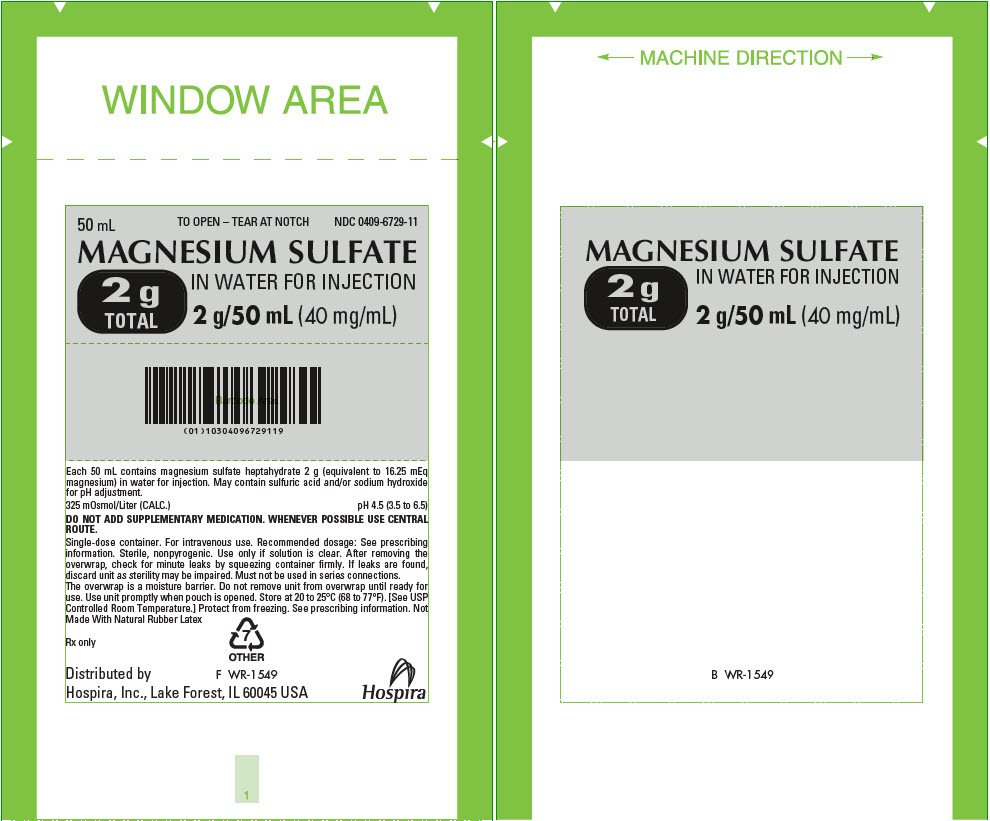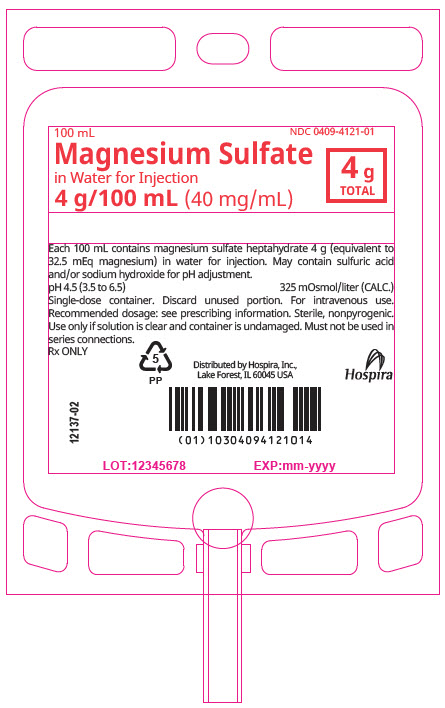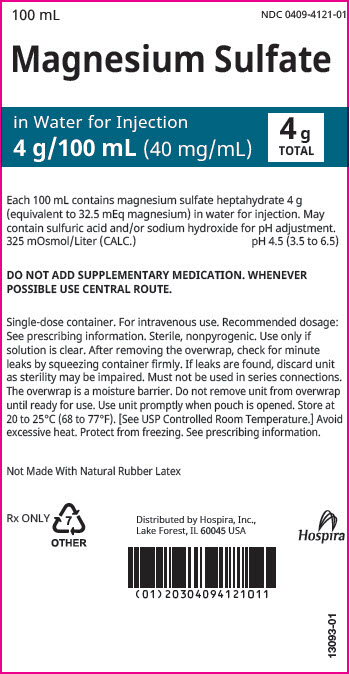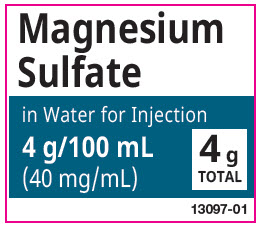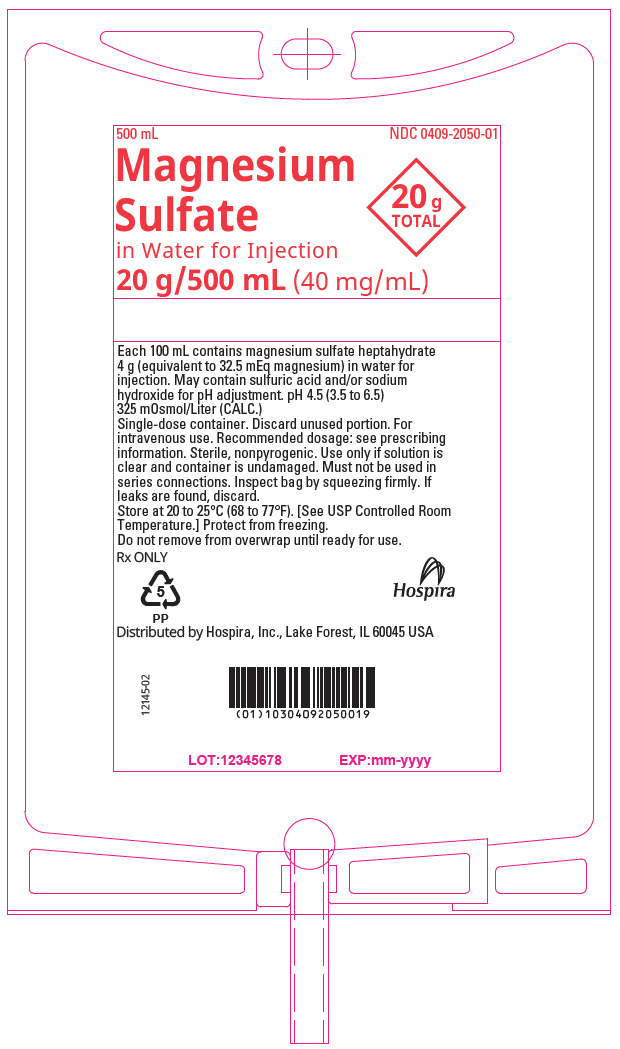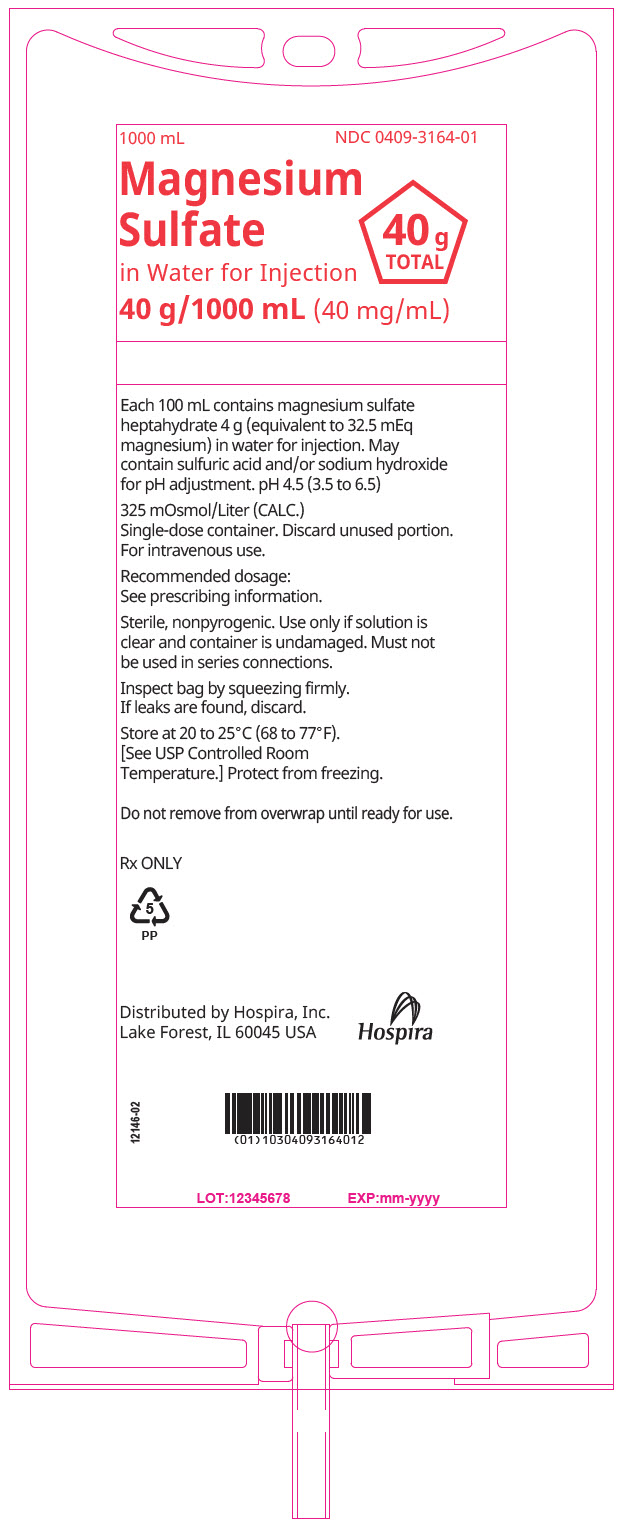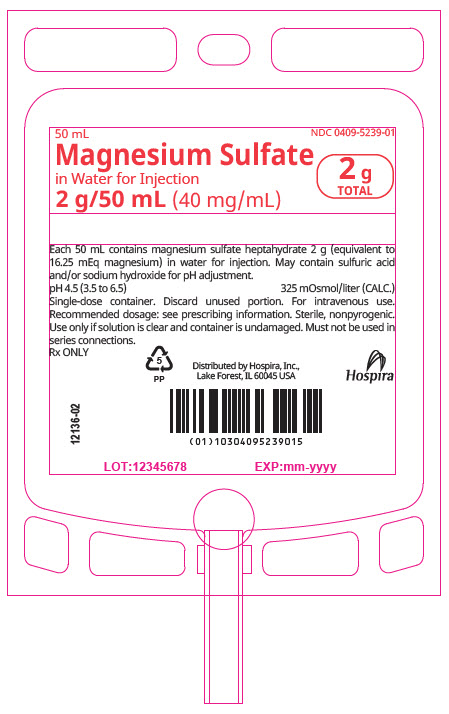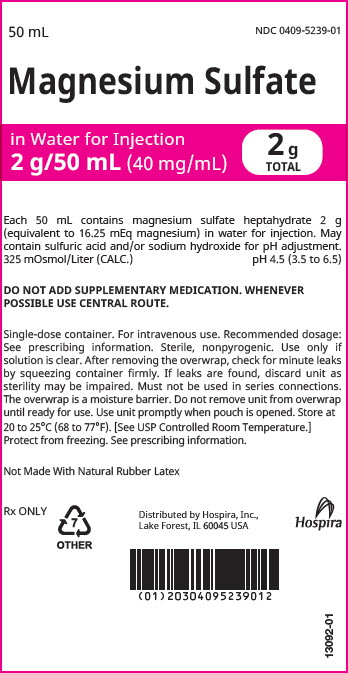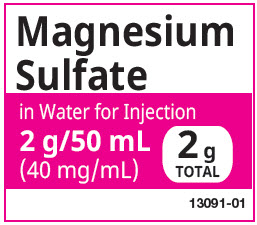 DRUG LABEL: Magnesium Sulfate in Water
NDC: 0409-6730 | Form: INJECTION, SOLUTION
Manufacturer: Hospira, Inc.
Category: prescription | Type: HUMAN PRESCRIPTION DRUG LABEL
Date: 20260211

ACTIVE INGREDIENTS: MAGNESIUM SULFATE HEPTAHYDRATE 80 mg/1 mL
INACTIVE INGREDIENTS: WATER; SULFURIC ACID; SODIUM HYDROXIDE

MAGNESIUM SULFATE
IN WATER FOR INJECTION

Flexible Plastic Container

For Intravenous Use Only

Rx only

DESCRIPTION

Magnesium Sulfate in Water for Injection is a sterile, nonpyrogenic solution of magnesium sulfate heptahydrate in water for injection. May contain sulfuric acid and/or sodium hydroxide for pH adjustment. The pH is 4.5 (3.5 to 6.5). It is available in 4% and 8% concentrations. See HOW SUPPLIED section for the content and characteristics of available dosage forms and sizes.

Magnesium Sulfate, USP heptahydrate is chemically designated MgSO4 • 7H2O, colorless crystals or white powder freely soluble in water.

Water for Injection, USP is chemically designated H2O.

Water can permeate from inside the flexible plastic container into the overwrap but not in amounts sufficient to affect the solution significantly. Solutions in contact with the plastic container may leach out certain chemical components from the plastic in very small amounts; however, biological testing was supportive of the safety of the plastic container materials. Exposure to temperatures above 25°C/77°F during transport and storage will lead to minor losses in moisture content. Higher temperatures lead to greater losses. It is unlikely that these minor losses will lead to clinically significant changes within the expiration period.

CLINICAL PHARMACOLOGY

Magnesium (Mg^++) is an important cofactor for enzymatic reactions and plays an important role in neurochemical transmission and muscular excitability.

Magnesium prevents or controls convulsions by blocking neuromuscular transmission and decreasing the amount of acetylcholine liberated at the end plate by the motor nerve impulse. Magnesium is said to have a depressant effect on the central nervous system, but it does not adversely affect the mother, fetus or neonate when used as directed in eclampsia or pre-eclampsia. Normal serum magnesium levels range from 1.3 to 2.1 mEq/liter.

As serum magnesium rises above 4 mEq/liter, the deep tendon reflexes are first decreased and then disappear as the serum level approaches 10 mEq/liter. At this level respiratory paralysis may occur. Heart block also may occur at this or lower serum levels of magnesium.

Magnesium acts peripherally to produce vasodilation. With low doses only flushing and sweating occur, but larger doses cause lowering of blood pressure. The central and peripheral effects of magnesium poisoning are antagonized to some extent by intravenous administration of calcium.

With intravenous administration the onset of anticonvulsant action is immediate and lasts about 30 minutes. Following intramuscular administration the onset of action occurs in about one hour and persists for three to four hours. Effective anticonvulsant serum levels range from 2.5 to 7.5 mEq/liter.

Pharmacokinetics:

Absorption: Intravenously administered magnesium is immediately absorbed.

Distribution: Approximately 1-2% of total body magnesium is located in the extracellular fluid space. Magnesium is 30% bound to albumin.

Metabolism: Magnesium is not metabolized.

Excretion: Magnesium is excreted solely by the kidney at a rate proportional to the serum concentration and glomerular filtration.

Special Populations:

Renal Insufficiency: Magnesium is excreted solely by the kidney. In patients with severe renal insufficiency, the dose should be lower and frequent serum magnesium levels must be obtained (see DOSAGE AND ADMINISTRATION).

Hepatic Insufficiency: Magnesium is excreted solely by the kidney. No dosing adjustments are necessary in hepatic insufficiency.

Drug-Drug Interactions: Drug induced renal losses of magnesium occur with the following drugs or drug classes:

Aminoglycosides

Cyclosporine

Digitalis

Alcohol

Amphotericin B

Diuretics

Cisplatin

INDICATIONS AND USAGE

Magnesium Sulfate in Water for Injection is indicated for the prevention and control of seizures in preeclampsia and eclampsia, respectively. When used judiciously it effectively prevents and controls the convulsions of eclampsia without producing deleterious depression of the central nervous system of the mother or infant. However, other effective drugs are available for this purpose.

CONTRAINDICATIONS

Intravenous magnesium should not be given to mothers with toxemia of pregnancy during the two hours preceding delivery.

WARNINGS

FETAL HARM: Continuous administration of magnesium sulfate beyond 5-7 days to pregnant women can lead to hypocalcemia and bone abnormalities in the developing fetus. These bone abnormalities include skeletal demineralization and osteopenia. In addition, cases of neonatal fracture have been reported. The shortest duration of treatment that can lead to fetal harm is not known. Magnesium sulfate should be used during pregnancy only if clearly needed. If magnesium sulfate is given for treatment of preterm labor, the woman should be informed that the efficacy and safety of such use have not been established and that use of magnesium sulfate beyond 5-7 days may cause fetal abnormalities.

Parenteral use in the presence of renal insufficiency may lead to magnesium intoxication.

PRECAUTIONS

Because magnesium is removed from the body solely by the kidneys, the drug should be used with caution in patients with renal impairment. Urine output should be maintained at a level of 100 mL every four hours. Monitoring serum magnesium levels and the patient’s clinical status is essential to avoid the consequences of overdosage in toxemia. Clinical indications of a safe dosage regimen include the presence of the patellar reflex (knee jerk) and absence of respiratory depression (approximately 16 breaths or more/minute). Serum magnesium levels usually sufficient to control convulsions range from 3 to 6 mg/100 mL (2.5 to 5 mEq/liter). The strength of the deep tendon reflexes begins to diminish when serum magnesium levels exceed 4 mEq/liter. Reflexes may be absent at 10 mEq magnesium/liter, where respiratory paralysis is a potential hazard. An injectable calcium salt should be immediately available to counteract the potential hazards of magnesium intoxication in eclampsia.

Magnesium Sulfate in Water for Injection should be administered slowly to avoid producing hypermagnesemia.

Carcinogenesis, Mutagenesis, Impairment of Fertility

Studies with Magnesium Sulfate in Water for Injection have not been performed to evaluate carcinogenic potential, mutagenic potential or effects on fertility.

Pregnancy

(See WARNINGS and PRECAUTIONS)

Teratogenic Effects

Magnesium Sulfate in Water for Injection, can cause fetal abnormalities when administered beyond 5-7 days to pregnant women. There are retrospective epidemiological studies and case reports documenting fetal abnormalities such as hypocalcemia, skeletal demineralization’s, osteopenia and other l skeletal abnormalities with continuous maternal administration of magnesium sulfate for more than 5-7 days.^1-12 Magnesium Sulfate in Water for Injection should be used during pregnancy only if clearly needed. If this drug is used during pregnancy the woman should be apprised of the potential harm to the fetus.

Nonteratogenic Effects

When administered by continuous IV infusion (especially for more than 24 hours preceding delivery) to control convulsions in a toxemic woman, the newborn may show signs of magnesium toxicity, including neuromuscular or respiratory depression. (See OVERDOSAGE.)

Labor and Delivery

Continuous administration of magnesium sulfate is an unapproved treatment for preterm labor. The safety and efficacy of such use have not been established. The administration of Magnesium Sulfate in Water for Injection outside of its approved indication in pregnant women should be by trained obstetrical personnel in a hospital setting with appropriate obstetrical care facilities.

Nursing Mothers

It is not known whether this drug is excreted in human milk. Because many drugs are excreted in human milk, caution should be exercised when Magnesium Sulfate in Water for Injection is administered to a nursing mother.

ADVERSE REACTIONS

The adverse effects of parenterally administered magnesium usually are the result of magnesium intoxication. These include flushing, sweating, hypotension, depressed reflexes, flaccid paralysis, hypothermia, circulatory collapse, cardiac and central nervous system depression proceeding to respiratory paralysis.

Hypocalcemia with signs of tetany secondary to magnesium sulfate therapy for eclampsia has been reported.

OVERDOSAGE

Magnesium intoxication is manifested by a sharp drop in blood pressure and respiratory paralysis. Disappearance of the patellar reflex is a useful clinical sign to detect the onset of magnesium intoxication. In the event of overdosage, artificial ventilation must be provided until a calcium salt can be injected IV to antagonize the effects of magnesium.

For Treatment of Overdose

Artificial respiration is often required. Intravenous calcium, 10 to 20 mL of a 5% solution (diluted if desirable) with isotonic sodium chloride for injection) is used to counteract effects of hypermagnesemia. Subcutaneous physostigmine, 0.5 to 1 mg may be helpful.

Hypermagnesemia in the newborn may require resuscitation and assisted ventilation via endotracheal intubation or intermittent positive pressure ventilation as well as IV calcium.

DOSAGE AND ADMINISTRATION

Magnesium Sulfate in Water for Injection is intended for intravenous use only. For the management of pre-eclampsia or eclampsia, intravenous infusions of dilute solutions of magnesium (1% to 8%) are often given in combination with intramuscular injections of 50% Magnesium Sulfate Injection, USP. Therefore, in the clinical conditions cited below, both forms of therapy are noted, as appropriate.

Continuous maternal administration of magnesium sulfate in pregnancy beyond 5-7 days can cause fetal abnormalities.

In Eclampsia

In severe pre-eclampsia or eclampsia, the total initial dose is 10 to 14 g of magnesium sulfate. To initiate therapy, 4 g of Magnesium Sulfate in Water for Injection may be administered intravenously. The rate of I.V. infusion should generally not exceed 150 mg/minute, or 3.75 mL of a 4% concentration (or its equivalent) per minute, except in severe eclampsia with seizures. Simultaneously, 4 to 5 g (32.5 to 40.6 mEq) of magnesium sulfate may be administered intramuscularly into each buttock using undiluted 50% Magnesium Sulfate Injection, USP. After the initial I.V. dose, some clinicians administer 1 to 2 g/hour by constant I.V. infusion.

Subsequent intramuscular doses of 4 to 5 g of magnesium sulfate may be injected into alternate buttocks every four hours, depending on the continuing presence of the patellar reflex, adequate respiratory function, and absence of signs of magnesium toxicity. Therapy should continue until paroxysms cease.

A serum magnesium level of 6 mg/100 mL is considered optimal for control of seizures. A total daily (24 hr) dose of 30 to 40 g magnesium sulfate should not be exceeded. In the presence of severe renal insufficiency, frequent serum magnesium concentrations must be obtained and the maximum dosage of magnesium sulfate is 20 g per 48 hours.

Parenteral drug products should be inspected visually for particulate matter and discoloration prior to administration, whenever solution and container permit.

Do not administer unless solution is clear. Discard unused portion.

HOW SUPPLIED

Magnesium Sulfate in Water for Injection is supplied in single-dose flexible plastic containers as follows:

NDC Number (Unit of Sale) | Concentration | Total Magnesium Sulfate [As the heptahydrate.] | Total Magnesium Ion | Magnesium Sulfate Concentration | Magnesium Ion Concentration | Osmolarity (calc.)
NDC 0409-6729-23; Case of 24 single-dose flexible plastic containers | 4 g/100 mL (40 mg/mL) | 4 g | 32.5 mEq | 4% (40 mg/mL) | 32.5 mEq/100 mL | 325 mOsmol/Liter
NDC 0409-4121-50; Case of 50 single-dose flexible plastic containers | 4 g/100 mL (40 mg/mL) | 4 g | 32.5 mEq | 4% (40 mg/mL) | 32.5 mEq/100 mL | 325 mOsmol/Liter
NDC 0409-6729-03; Case of 24 single-dose flexible plastic containers | 20 g/500 mL (40 mg/mL) | 20 g | 162.3 mEq | 4% (40 mg/mL) | 32.5 mEq/100 mL | 325 mOsmol/Liter
NDC 0409-2050-20; Case of 20 single-dose flexible plastic containers | 20 g/500 mL (40 mg/mL) | 20 g | 162.3 mEq | 4% (40 mg/mL) | 32.5 mEq/100 mL | 325 mOsmol/Liter
NDC 0409-6729-09; Case of 12 single-dose flexible plastic containers | 40 g/1000 mL (40 mg/mL) | 40 g | 325 mEq | 4% (40 mg/mL) | 32.5 mEq/100 mL | 325 mOsmol/Liter
NDC 0409-3164-12; Case of 12 single-dose flexible plastic containers | 40 g/1000 mL (40 mg/mL) | 40 g | 325 mEq | 4% (40 mg/mL) | 32.5 mEq/100 mL | 325 mOsmol/Liter
NDC 0409-6729-24; Case of 24 single-dose flexible plastic containers | 2 g/50 mL [Partial fill container 50 mL volume in 100 mL container.] (40 mg/mL) | 2 g | 16.25 mEq | 4% (40 mg/mL) | 16.25 mEq/50 mL | 325 mOsmol/Liter
NDC 0409-5239-60; Case of 60 single-dose flexible plastic containers | 2 g/50 mL (40 mg/mL) | 2 g | 16.25 mEq | 4% (40 mg/mL) | 16.25 mEq/50 mL | 325 mOsmol/Liter
NDC 0409-6730-13; Case of 24 single-dose flexible plastic containers | 4 g/50 mL (80 mg/mL) | 4 g | 32.5 mEq | 8% (80 mg/mL) | 32.5 mEq/50 mL | 649 mOsmol/Liter
NDC 0409-6730-60; Case of 60 single-dose flexible plastic containers | 4 g/50 mL (80 mg/mL) | 4 g | 32.5 mEq | 8% (80 mg/mL) | 32.5 mEq/50 mL | 649 mOsmol/Liter

WARNING: DO NOT USE FLEXIBLE CONTAINER IN SERIES CONNECTIONS.

Store at 20 to 25°C (68 to 77°F). [See USP Controlled Room Temperature.] Protect from freezing.

REFERENCES

1. Yokoyama K, Takahashi N, Yada Y. Prolonged maternal magnesium administration and bone metabolism in neonates. Early Human Dev. 2010; 86(3):187-91. Epub 2010 Mar 12.
2. Wedig KE, Kogan J, Schorry EK et al. Skeletal demineralization and fractures caused by fetal magnesium toxicity. J Perinatol. 2006; 26(6):371-4.
3. Nassar AH, Sakhel K, Maarouf H, et al. Adverse maternal and neonatal outcome of prolonged course of magnesium sulfate tocolysis. Acta Obstet Gynecol Scan. 2006;85(9):1099-103.
4. Malaeb SN, Rassi A, Haddad MC. Bone mineralization in newborns whose mothers received magnesium sulphate for tocolysis of premature labor. Pediatr Radiol. 2004;34(5):384-6. Epub 2004 Feb 18.
5. Matsuda Y, Maeda Y, Ito M, et al. Effect of magnesium sulfate treatment on neonatal bone abnormalities. Gynecol Obstet Invest. 1997; 44(2):82-8.
6. Schanler RJ, Smith LG, Burns PA. Effects of long-term maternal intravenous magnesium sulfate therapy on neonatal calcium metabolism and bone mineral content. Gynecol Obstet Invest. 1997; 43(4):236-41.
7. Santi MD, Henry GW, Douglas GL. Magnesium sulfate treatment of preterm labor as a cause of abnormal neonatal bone mineralization. J Pediatr Orthop. 1994; 14(2):249-53.
8. Holocomb WL, Shackelford GD, Petrie RH. Magnesium tocolysis and neonatal bone abnormalities: a controlled study. Obstet Gynecol. 1991; 78(4):611-4.
9. Cumming WA, Thomas VJ. Hypermagnesemia: a cause of abnormal metaphyses in the neonate. Am J Roentgenol. 1989; 152(5):1071-2.
10. Lamm CL, Norton KL, Murphy RJ. Congenital rickets associated with magnesium sulfate infusion for tocolysis. J Pediatr. 1988; 113(6):1078-82.
11. McGuinness GA, Weinstein MM, Cruikshank DP, et al. Effects of magnesium sulfate treatment on perinatal calcium metabolism. II. Neonatal responses. Obstet Gynecol. 1980;56(5):595-600.
12. Riaz M, Porat R, Brodsky NL, et al. The effect of maternal magnesium sulfate treatment on newborns: a prospective controlled study. J Perinatol. 1998; 18(6 pt 1):449-54.

Distributed by Hospira, Inc., Lake Forest, IL 60045 USA

LAB-1087-3.0

Revised: 03/2022

PRINCIPAL DISPLAY PANEL - 50 mL Bag Label

50 mL
NDC 0409-6730-11

MAGNESIUM SULFATE
IN WATER FOR INJECTION
4 g/50 mL (80 mg/mL)

4g
TOTAL

EACH 50 mL CONTAINS MAGNESIUM SULFATE
HEPTAHYDRATE 4 g (EQUIVALENT TO 32.5 mEq
MAGNESIUM) IN WATER FOR INJECTION. MAY
CONTAIN SULFURIC ACID AND/OR SODIUM
HYDROXIDE FOR pH ADJUSTMENT.
pH 4.5 (3.5 to 6.5) 649 mOsmol/LITER (CALC.)
SINGLE-DOSE CONTAINER. DISCARD UNUSED
PORTION. FOR INTRAVENOUS USE.
RECOMMENDED DOSAGE: SEE PRESCRIBING
INFORMATION. STERILE, NONPYROGENIC. USE
ONLY IF SOLUTION IS CLEAR AND CONTAINER IS
UNDAMAGED. MUST NOT BE USED IN SERIES
CONNECTIONS.

Rx ONLY

IM-5199

3
V
CONTAINS DEHP

Hospira

DISTRIBUTED BY
HOSPIRA, INC., LAKE FOREST, IL 60045 USA

PRINCIPAL DISPLAY PANEL - 50 mL Bag Pouch Label

50 mL
TO OPEN – TEAR AT NOTCH
NDC 0409-6730-11

MAGNESIUM SULFATE
IN WATER FOR INJECTION

4 g/50 mL (80 mg/mL)

4g
TOTAL

Each 50 mL contains magnesium sulfate heptahydrate 4 g (equivalent to 32.5 mEq
magnesium) in water for injection. May contain sulfuric acid and/or sodium hydroxide
for pH adjustment.

649 mOsmol/Liter (CALC.)
pH 4.5 (3.5 to 6.5)

DO NOT ADD SUPPLEMENTARY MEDICATION. WHENEVER POSSIBLE USE CENTRAL
ROUTE.

Single-dose container. For intravenous use. Recommended dosage: See prescribing
information. Sterile, nonpyrogenic. Use only if solution is clear. After removing the
overwrap, check for minute leaks by squeezing container firmly. If leaks are found,
discard unit as sterility may be impaired. Must not be used in series connections.
The overwrap is a moisture barrier. Do not remove unit from overwrap until ready for
use. Use unit promptly when pouch is opened. Store at 20 to 25°C (68 to 77°F). [See USP
Controlled Room Temperature.] Protect from freezing. See prescribing information.
Not Made With Natural Rubber Latex.

Rx only

7
OTHER

Distributed by
Hospira, Inc., Lake Forest, IL 60045 USA

F WR-1551

Hospira

PRINCIPAL DISPLAY PANEL - 50 mL Bag Label - NDC 0409-6730-50

50 mL
NDC 0409-6730-50
Magnesium Sulfate
in Water for Injection
4 g/50 mL (80 mg/mL)
4g
TOTAL

Each 50 mL contains magnesium sulfate heptahydrate 4 g (equivalent to
32.5 mEq magnesium) in water for injection. May contain sulfuric acid
and/or sodium hydroxide for pH adjustment.
pH 4.5 (3.5 to 6.5)
649 mOsmol/Liter (CALC.)
Single-dose container. Discard unused portion. For intravenous use.
Recommended dosage: See prescribing information. Sterile, nonpyrogenic.
Use only if solution is clear and container is undamaged. Must not be used in
series connections.

Rx ONLY

5
PP

Distributed by Hospira, Inc.,
Lake Forest, IL 60045 USA

Hospira

12165-02

LOT:12345678
EXP:mm-yyyy

PRINCIPAL DISPLAY PANEL - 50 mL Bag Pouch Label - NDC 0409-6730-50

50 mL
NDC 0409-6730-50

Magnesium Sulfate

in Water for Injection
4 g/50 mL (80 mg/mL)
4 g
TOTAL

Each 50 mL contains magnesium sulfate heptahydrate 4 g
(equivalent to 32.5 mEq magnesium) in water for injection. May
contain sulfuric acid and/or sodium hydroxide for pH adjustment.
649 mOsmol/Liter (CALC.)
pH 4.5 (3.5 to 6.5)

DO NOT ADD SUPPLEMENTARY MEDICATION. WHENEVER
POSSIBLE USE CENTRAL ROUTE.

Single-dose container. For intravenous use. Recommended dosage:
See prescribing information. Sterile, nonpyrogenic. Use only if
solution is clear. After removing the overwrap, check for minute
leaks by squeezing container firmly. If leaks are found, discard unit
as sterility may be impaired. Must not be used in series connections.
The overwrap is a moisture barrier. Do not remove unit from
overwrap until ready for use. Use unit promptly when pouch is
opened. Store at 20 to 25°C (68 to 77°F). [See USP Controlled Room
Temperature.] Protect from freezing. See prescribing information.

Not Made With Natural Rubber Latex.

Rx ONLY

7
OTHER

Distributed by Hospira, Inc.,
Lake Forest, IL 60045 USA

Hospira

13090-01

PRINCIPAL DISPLAY PANEL - 50 mL Bag Overwrap Back

Magnesium
Sulfate

in Water for Injection
4 g/50 mL
(80 mg/mL)
4 g
TOTAL

13088-01

PRINCIPAL DISPLAY PANEL - 100 mL Bag Label

100 mL
NDC 0409-6729-41

MAGNESIUM SULFATE
IN WATER FOR INJECTION

4 g/100 mL (40 mg/mL)

4g
TOTAL

EACH 100 mL CONTAINS MAGNESIUM SULFATE
HEPTAHYDRATE 4 g (EQUIVALENT TO 32.5 mEq
MAGNESIUM) IN WATER FOR INJECTION. MAY
CONTAIN SULFURIC ACID AND/OR SODIUM
HYDROXIDE FOR pH ADJUSTMENT.
pH 4.5 (3.5 to 6.5) 325 mOsmol/LITER (CALC.)
SINGLE-DOSE CONTAINER. DISCARD UNUSED
PORTION. FOR INTRAVENOUS USE.
RECOMMENDED DOSAGE: SEE PRESCRIBING
INFORMATION. STERILE, NONPYROGENIC. USE
ONLY IF SOLUTION IS CLEAR AND CONTAINER IS
UNDAMAGED. MUST NOT BE USED IN SERIES
CONNECTIONS.

Rx ONLY

IM-5198

3
V
CONTAINS DEHP

Hospira

DISTRIBUTED BY
HOSPIRA, INC., LAKE FOREST, IL 60045 USA

PRINCIPAL DISPLAY PANEL - 100 mL Bag Pouch Label

100 mL
TO OPEN – TEAR AT NOTCH
NDC 0409-6729-41

MAGNESIUM SULFATE
IN WATER FOR INJECTION

4 g/100 mL (40 mg/mL)

4g
TOTAL

Each 100 mL contains magnesium sulfate heptahydrate 4 g (equivalent to 32.5 mEq
magnesium) in water for injection. May contain sulfuric acid and/or sodium hydroxide
for pH adjustment.

325 mOsmol/Liter (CALC.)
pH 4.5 (3.5 to 6.5)

DO NOT ADD SUPPLEMENTARY MEDICATION. WHENEVER POSSIBLE USE CENTRAL
ROUTE.

Single-dose container. For intravenous use. Recommended dosage: See prescribing
information. Sterile, nonpyrogenic. Use only if solution is clear. After removing the
overwrap, check for minute leaks by squeezing container firmly. If leaks are found,
discard unit as sterility may be impaired. Must not be used in series connections.
The overwrap is a moisture barrier. Do not remove unit from overwrap until ready for
use. Use unit promptly when pouch is opened. Store at 20 to 25°C (68 to 77°F). [See USP
Controlled Room Temperature.] Avoid excessive heat. Protect from freezing. See
prescribing information.
Not Made With Natural Rubber Latex.

Rx only

7
OTHER

Distributed by
Hospira, Inc., Lake Forest, IL 60045 USA

F WR-1550

Hospira

PRINCIPAL DISPLAY PANEL - 500 mL Bag Label

500 mL
NDC 0409-6729-21

20 g
TOTAL

MAGNESIUM
SULFATE

IN WATER FOR INJECTION
20 g/500 mL (40 mg/mL)

EACH 100 mL CONTAINS MAGNESIUM SULFATE
HEPTAHYDRATE 4 g (EQUIVALENT TO 32.5 mEq
MAGNESIUM) IN WATER FOR INJECTION. MAY CONTAIN
SULFURIC ACID AND/OR SODIUM HYDROXIDE FOR pH
ADJUSTMENT.

pH 4.5 (3.5 to 6.5)
325 mOsmol/LlTER (CALC.)

SINGLE-DOSE CONTAINER. DISCARD UNUSED PORTION.
FOR INTRAVENOUS USE. RECOMMENDED DOSAGE: SEE
PRESCRIBING INFORMATION. STERILE, NONPYROGENIC.
USE ONLY IF SOLUTION IS CLEAR AND CONTAINER IS
UNDAMAGED. MUST NOT BE USED IN SERIES
CONNECTIONS.

Rx ONLY

3
V
CONTAINS DEHP

Hospira

IM-5196

DISTRIBUTED BY
HOSPIRA, INC., LAKE FOREST, IL 60045 USA

PRINCIPAL DISPLAY PANEL - 40 mg/mL Bag Overwrap - 500 mL

TO OPEN TEAR AT NOTCH

2
HDPE

DO NOT REMOVE FROM OVERWRAP UNTIL READY FOR USE. AFTER REMOVING
THE OVERWRAP, CHECK FOR MINUTE LEAKS BY SQUEEZING CONTAINER FIRMLY.
IF LEAKS ARE FOUND, DISCARD SOLUTION AS STERILITY MAY BE IMPAIRED.
RECOMMENDED STORAGE: ROOM TEMPERATURE (25°C). AVOID EXCESSIVE
HEAT. PROTECT FROM FREEZING. SEE INSERT.
98-4321-R14-3/98

PRINCIPAL DISPLAY PANEL - 1000 mL Bag Label

1000 mL
NDC 0409-6729-31

MAGNESIUM
SULFATE
IN WATER FOR
INJECTION

40 g
TOTAL

40 g/1000 mL (40 mg/mL)

EACH 100 mL CONTAINS MAGNESIUM
SULFATE HEPTAHYDRATE 4 g (EQUIVALENT
TO 32.5 mEq MAGNESIUM) IN WATER FOR
INJECTION. MAY CONTAIN SULFURIC ACID
AND/OR SODIUM HYDROXIDE FOR pH
ADJUSTMENT.

pH 4.5 (3.5 to 6.5)
325 mOsmol/LITER (CALC.)

SINGLE-DOSE CONTAINER. DISCARD
UNUSED PORTION. FOR INTRAVENOUS
USE. RECOMMENDED DOSAGE: SEE
PRESCRIBING INFORMATION. STERILE,
NONPYROGENIC. USE ONLY IF SOLUTION
IS CLEAR AND CONTAINER IS
UNDAMAGED. MUST NOT BE USED IN
SERIES CONNECTIONS.

Rx ONLY

3
V
CONTAINS DEHP

DISTRIBUTED BY
HOSPIRA, INC., LAKE FOREST, IL 60045 USA

IM-5197

Hospira

PRINCIPAL DISPLAY PANEL - 40 mg/mL Bag Overwrap - 1000 mL

TO OPEN TEAR AT NOTCH

2
HDPE

DO NOT REMOVE FROM OVERWRAP UNTIL READY FOR USE. AFTER REMOVING
THE OVERWRAP, CHECK FOR MINUTE LEAKS BY SQUEEZING CONTAINER FIRMLY.
IF LEAKS ARE FOUND, DISCARD SOLUTION AS STERILITY MAY BE IMPAIRED.
RECOMMENDED STORAGE: ROOM TEMPERATURE (25°C). AVOID EXCESSIVE
HEAT. PROTECT FROM FREEZING. SEE INSERT.
98-4321-R14-3/98

PRINCIPAL DISPLAY PANEL - 2 g/50 mL Bag Label

50 mL
NDC 0409-6729-11

MAGNESIUM SULFATE
IN WATER FOR INJECTION

2g
TOTAL

2 g/50 mL (40 mg/mL)

EACH 50 mL CONTAINS MAGNESIUM SULFATE
HEPTAHYDRATE 2 g (EQUIVALENT TO 16.25 mEq
MAGNESIUM) IN WATER FOR INJECTION. MAY
CONTAIN SULFURIC ACID AND/OR SODIUM
HYDROXIDE FOR pH ADJUSTMENT.

pH 4.5 (3.5 to 6.5) 325 mOsmol/LITER (CALC.)

SINGLE-DOSE CONTAINER. DISCARD UNUSED
PORTION. FOR INTRAVENOUS USE.
RECOMMENDED DOSAGE: SEE PRESCRIBING
INFORMATION. STERILE, NONPYROGENIC. USE
ONLY IF SOLUTION IS CLEAR AND CONTAINER IS
UNDAMAGED. MUST NOT BE USED IN SERIES
CONNECTIONS.

Rx ONLY

3
V
CONTAINS DEHP

Hospira

IM-5195

DISTRIBUTED BY HOSPIRA, INC.,
LAKE FOREST, IL 60045 USA

PRINCIPAL DISPLAY PANEL - 2 g/50 mL Bag Pouch Label

50 mL
TO OPEN – TEAR AT NOTCH
NDC 0409-6729-11

MAGNESIUM SULFATE
IN WATER FOR INJECTION

2 g
TOTAL

2 g/50 mL (40 mg/mL)

Each 50 mL contains magnesium sulfate heptahydrate 2 g (equivalent to 16.25 mEq
magnesium) in water for injection. May contain sulfuric acid and/or sodium hydroxide
for pH adjustment.

325 mOsmol/Liter (CALC.)
pH 4.5 (3.5 to 6.5)

DO NOT ADD SUPPLEMENTARY MEDICATION. WHENEVER POSSIBLE USE CENTRAL
ROUTE.

Single-dose container. For intravenous use. Recommended dosage: See prescribing
information. Sterile, nonpyrogenic. Use only if solution is clear. After removing the
overwrap, check for minute leaks by squeezing container firmly. If leaks are found,
discard unit as sterility may be impaired. Must not be used in series connections.
The overwrap is a moisture barrier. Do not remove unit from overwrap until ready for
use. Use unit promptly when pouch is opened. Store at 20 to 25°C (68 to 77°F). [See USP
Controlled Room Temperature.] Protect from freezing. See prescribing information. Not
Made With Natural Rubber Latex

Rx only

7
OTHER

Distributed by
Hospira, Inc., Lake Forest, IL 60045 USA

F WR-1549

Hospira

PRINCIPAL DISPLAY PANEL - 4 g/100 mL Bag Label

100 mL
NDC 0409-4121-01

Magnesium Sulfate
in Water for Injection

4 g
TOTAL

4 g/100 mL (40 mg/mL)

Each 100 mL contains magnesium sulfate heptahydrate 4 g (equivalent to
32.5 mEq magnesium) in water for injection. May contain sulfuric acid
and/or sodium hydroxide for pH adjustment.

pH 4.5 (3.5 to 6.5)
325 mOsmol/liter (CALC.)

Single-dose container. Discard unused portion. For intravenous use.
Recommended dosage: see prescribing information. Sterile, nonpyrogenic.
Use only if solution is clear and container is undamaged. Must not be used in
series connections.

Rx ONLY

5
PP

Distributed by Hospira, Inc.,
Lake Forest, IL 60045 USA

Hospira

12137-02

LOT:12345678
EXP:mm-yyyy

PRINCIPAL DISPLAY PANEL - 4 g/100 mL Bag Pouch Label

100 mL
NDC 0409-4121-01

Magnesium Sulfate

in Water for Injection
4 g/100 mL (40 mg/mL)

4 g
TOTAL

Each 100 mL contains magnesium sulfate heptahydrate 4 g
(equivalent to 32.5 mEq magnesium) in water for injection. May
contain sulfuric acid and/or sodium hydroxide for pH adjustment.

325 mOsmol/Liter (CALC.)
pH 4.5 (3.5 to 6.5)

DO NOT ADD SUPPLEMENTARY MEDICATION. WHENEVER
POSSIBLE USE CENTRAL ROUTE.

Single-dose container. For intravenous use. Recommended dosage:
See prescribing information. Sterile, nonpyrogenic. Use only if
solution is clear. After removing the overwrap, check for minute
leaks by squeezing container firmly. If leaks are found, discard unit
as sterility may be impaired. Must not be used in series connections.
The overwrap is a moisture barrier. Do not remove unit from overwrap
until ready for use. Use unit promptly when pouch is opened. Store at
20 to 25°C (68 to 77°F). [See USP Controlled Room Temperature.] Avoid
excessive heat. Protect from freezing. See prescribing information.

Not Made With Natural Rubber Latex

Rx ONLY

7
OTHER

Distributed by Hospira, Inc.,
Lake Forest, IL 60045 USA

Hospira

13093-01

PRINCIPAL DISPLAY PANEL - 100 mL Bag Overwrap Back

Magnesium
Sulfate

in Water for Injection
4 g/100 mL
(40 mg/mL)
4 g
TOTAL

13097-01

PRINCIPAL DISPLAY PANEL - 20 g/500 mL Bag Label

500 mL
NDC 0409-2050-01

Magnesium
Sulfate
in Water for Injection

20 g
TOTAL

20 g/500 mL (40 mg/mL)

Each 100 mL contains magnesium sulfate heptahydrate
4 g (equivalent to 32.5 mEq magnesium) in water for
injection. May contain sulfuric acid and/or sodium
hydroxide for pH adjustment. pH 4.5 (3.5 to 6.5)
325 mOsmol/Liter (CALC.)
Single-dose container. Discard unused portion. For
intravenous use. Recommended dosage: see prescribing
information. Sterile, nonpyrogenic. Use only if solution is
clear and container is undamaged. Must not be used in
series connections. Inspect bag by squeezing firmly. If
leaks are found, discard.
Store at 20 to 25°C (68 to 77°F). [See USP Controlled Room
Temperature.] Protect from freezing.
Do not remove from overwrap until ready for use.

Rx ONLY

5
PP

Hospira

Distributed by Hospira, Inc., Lake Forest, IL 60045 USA

12145-02

LOT:12345678
EXP:mm-yyyy

PRINCIPAL DISPLAY PANEL - 40 g/1000 mL Bag Label

1000 mL
NDC 0409-3164-01

Magnesium
Sulfate
in Water for Injection

40 g
TOTAL

40 g/1000 mL (40 mg/mL)

Each 100 mL contains magnesium sulfate
heptahydrate 4 g (equivalent to 32.5 mEq
magnesium) in water for injection. May
contain sulfuric acid and/or sodium hydroxide
for pH adjustment. pH 4.5 (3.5 to 6.5)

325 mOsmol/Liter (CALC.)
Single-dose container. Discard unused portion.
For intravenous use.

Recommended dosage:
See prescribing information.

Sterile, nonpyrogenic. Use only if solution is
clear and container is undamaged. Must not
be used in series connections.

Inspect bag by squeezing firmly.
If leaks are found, discard.

Store at 20 to 25°C (68 to 77°F).
[See USP Controlled Room
Temperature.] Protect from freezing.

Do not remove from overwrap until ready for use.

Rx ONLY

5
PP

Distributed by Hospira, Inc.
Lake Forest, IL 60045 USA

Hospira

12146-02

LOT:12345678
EXP:mm-yyyy

PRINCIPAL DISPLAY PANEL -2 g/50 mL Bag Label - 0409-5239

50 mL
NDC 0409-5239-01

Magnesium Sulfate
in Water for Injection

2 g
TOTAL

2 g/50 mL (40 mg/mL)

Each 50 mL contains magnesium sulfate heptahydrate 2 g (equivalent to
16.25 mEq magnesium) in water for injection. May contain sulfuric acid
and/or sodium hydroxide for pH adjustment.

pH 4.5 (3.5 to 6.5)
325 mOsmol/liter (CALC.)

Single-dose container. Discard unused portion. For intravenous use.
Recommended dosage: see prescribing information. Sterile, nonpyrogenic.
Use only if solution is clear and container is undamaged. Must not be used in
series connections.

Rx ONLY

5
PP

Distributed by Hospira, Inc.,
Lake Forest, IL 60045 USA

Hospira

12136-02

LOT:12345678
EXP:mm-yyyy

PRINCIPAL DISPLAY PANEL -2 g/50 mL Bag Pouch Label - 0409-5239

50 mL
NDC 0409-5239-01

Magnesium Sulfate

in Water for Injection
2 g/50 mL (40 mg/mL)

2 g
TOTAL

Each 50 mL contains magnesium sulfate heptahydrate 2 g
(equivalent to 16.25 mEq magnesium) in water for injection. May
contain sulfuric acid and/or sodium hydroxide for pH adjustment.

325 mOsmol/Liter (CALC.)
pH 4.5 (3.5 to 6.5)

DO NOT ADD SUPPLEMENTARY MEDICATION. WHENEVER
POSSIBLE USE CENTRAL ROUTE.

Single-dose container. For intravenous use. Recommended dosage:
See prescribing information. Sterile, nonpyrogenic. Use only if
solution is clear. After removing the overwrap, check for minute leaks
by squeezing container firmly. If leaks are found, discard unit as
sterility may be impaired. Must not be used in series connections.
The overwrap is a moisture barrier. Do not remove unit from overwrap
until ready for use. Use unit promptly when pouch is opened. Store at
20 to 25°C (68 to 77°F). [See USP Controlled Room Temperature.]
Protect from freezing. See prescribing information.

Not Made With Natural Rubber Latex

Rx ONLY

7
OTHER

Distributed by Hospira, Inc.,
Lake Forest, IL 60045 USA

Hospira

13092-01

PRINCIPAL DISPLAY PANEL - 2 g/50 mL Bag Overwrap Back

Magnesium
Sulfate

in Water for Injection
2 g/50 mL
(40 mg/mL)
2 g
TOTAL

13091-01